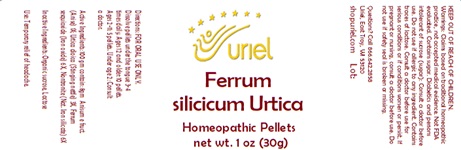 DRUG LABEL: Ferrum silicicum Urtica
NDC: 48951-4177 | Form: PELLET
Manufacturer: Uriel Pharmacy Inc.
Category: homeopathic | Type: HUMAN OTC DRUG LABEL
Date: 20231106

ACTIVE INGREDIENTS: ANISE 1 [hp_X]/1 1; URTICA DIOICA ROOT 3 [hp_X]/1 1; FERRIC OXIDE RED 6 [hp_X]/1 1; SILICON DIOXIDE 6 [hp_X]/1 1
INACTIVE INGREDIENTS: SUCROSE

Ferrum silicicum Urtica

INDICATIONS AND USAGE

Directions: FOR ORAL USE ONLY.

DOSAGE AND ADMINISTRATION

Dissolve pellets under the tongue 3-4 times daily. Ages 12 and older: 10 pellets. Ages 2-11: 5 pellets. Under age 2: Consult a doctor.

ACTIVE INGREDIENT

Active Ingredients: Anisum (Anise) 1X, Urtica dioica (Stinging nettle) 3X, Ferrum sesquioxide (Iron oxide) 6X, Nontronite (Nat. Iron silicate) 6X

Inactive Ingredient: Organic sucrose, Lactose

PURPOSE

Use: Temporary relief of headache.

KEEP OUT OF REACH OF CHILDREN.

WARNINGS

Warnings: Claims based on traditional homeopathic practice, not accepted medical evidence. Not FDA evaluated. Contains sugar. Diabetics and persons intolerant of sucrose (sugar): Consult a doctor before use. Do not use if allergic to any ingredient. Contains traces of Lactose. Consult a doctor before use for serious conditions or if conditions worsen or persist. If pregnant or nursing, consult a doctor before use. Do not use if safety seal is broken or missing.

QUESTIONS

Questions? Call 866.642.2858 Uriel, East Troy, WI 53120 shopuriel.com Lot: